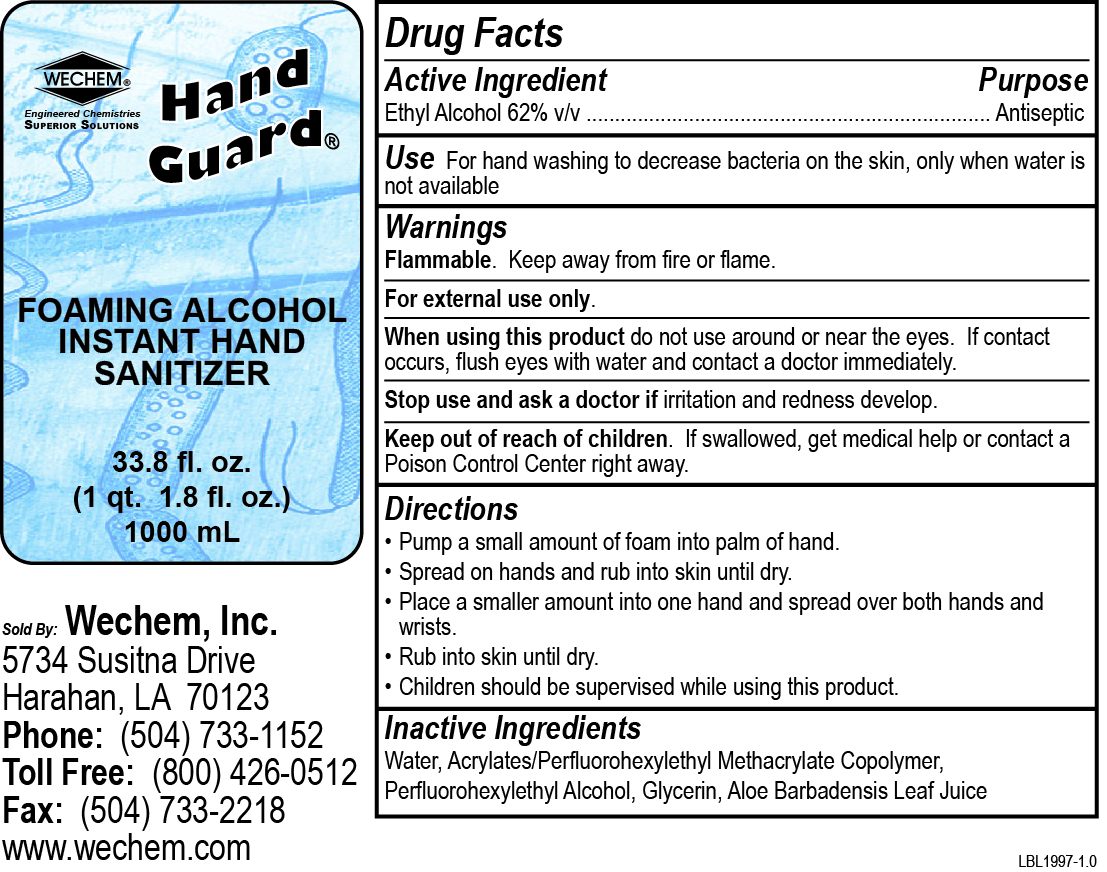 DRUG LABEL: Hand Guard Foaming Alcohol Instant Hand Sanitizer
NDC: 31507-024 | Form: SOLUTION
Manufacturer: Wechem, Inc.
Category: otc | Type: HUMAN OTC DRUG LABEL
Date: 20250110

ACTIVE INGREDIENTS: ALCOHOL 620 mL/1 L
INACTIVE INGREDIENTS: WATER; 2-(PERFLUOROHEXYL)ETHANOL; GLYCERIN; BUTYL ACRYLATE/METHYL METHACRYLATE/PERFLUOROHEXYLETHYL METHACRYLATE COPOLYMER (SALUS AF); ALOE VERA LEAF

Hand Guard Foaming Alcohol Instant Hand Sanitizer

Active Ingredient

Ethyl Alcohol 62% v/v

Purpose

Antiseptic

Use

For hand washing to decrease bacteria on the skin, only when water is not available

Warnings

Flammable. Keep away from fire or flame.

For external use only.

When using this product do not use around or near the eyes. If contact occurs, flush eyes with water and contact a doctor immediately.

Stop use and ask a doctor if irritation and redness develop.

Keep out of reach of children. If swallowed, get medical help or contact a Poison Control Center right away.

Directions

- Pump a small amount of foam into palm of hand.
- Spread on hands and rub into skin until dry.
- Place a smaller amount into one hand and spread over both hands and wrists.
- Rub into skin until dry.
- Children should be supervised while using this product.

Inactive Ingredients

Water, Acrylates/Perfluorohexylethyl Methacrylate Copolymer, Perfluorohexylethyl Alcohol, Glycerin, Aloe Barbadensis Leaf Juice